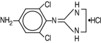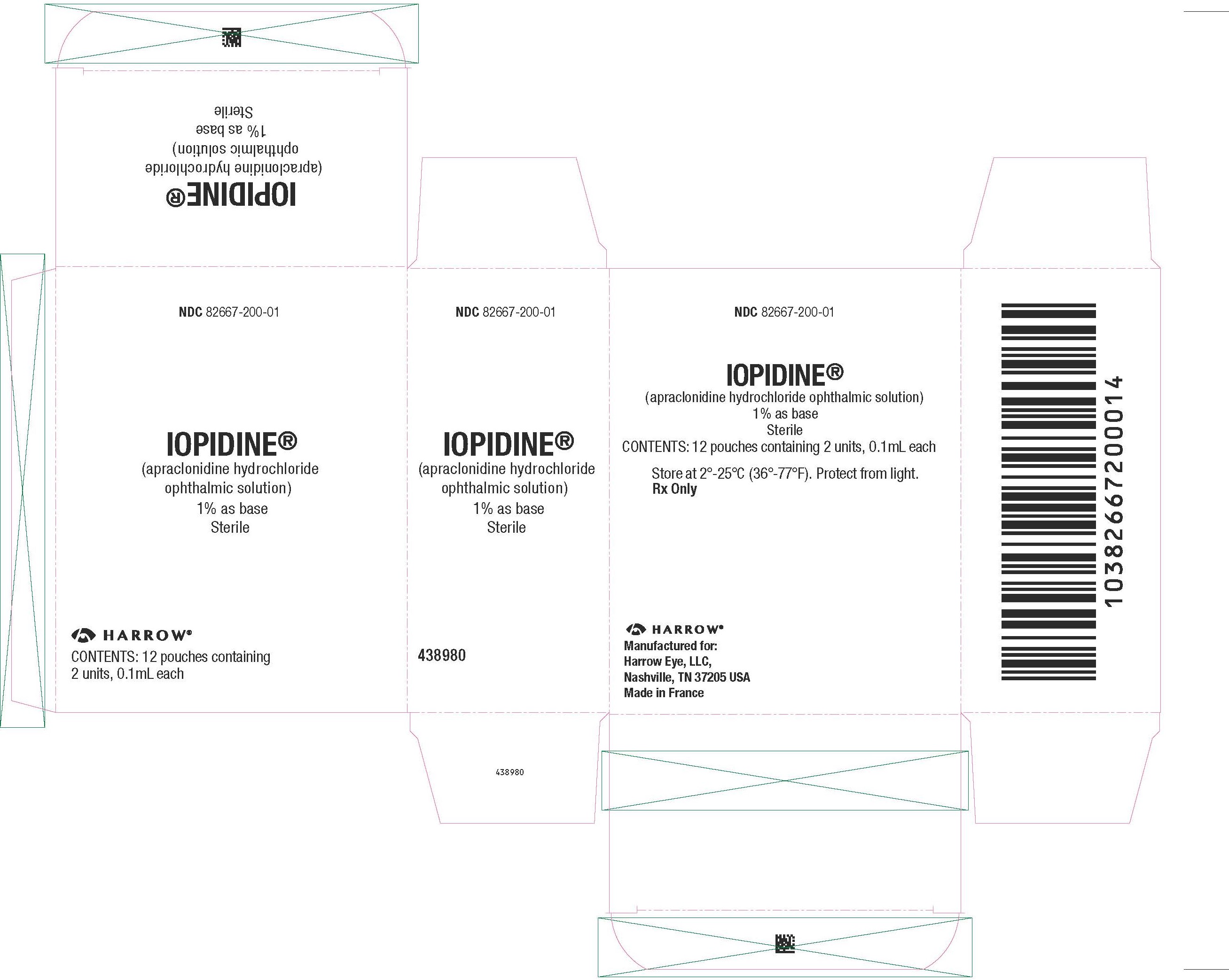 DRUG LABEL: IOPIDINE 1%
NDC: 82667-200 | Form: SOLUTION/ DROPS
Manufacturer: Harrow Eye, LLC
Category: prescription | Type: HUMAN PRESCRIPTION DRUG LABEL
Date: 20241219

ACTIVE INGREDIENTS: APRACLONIDINE HYDROCHLORIDE 10 mg/1 mL
INACTIVE INGREDIENTS: SODIUM CHLORIDE; WATER; HYDROCHLORIC ACID; BENZALKONIUM CHLORIDE; SODIUM ACETATE; SODIUM HYDROXIDE

IOPIDINE 1% (apraclonidine hydrochloride ophthalmic solution) 1% as base Sterile

DESCRIPTION

IOPIDINE 1% Ophthalmic Solution contains apraclonidine hydrochloride, an alpha adrenergic agonist, in a sterile isotonic solution
for topical application to the eye. Apraclonidine hydrochloride is a white to off‑white powder and is highly soluble in water. Its chemical name is 2-[(4‑amino-2,6 dichlorophenyl)imino] imidazolidine monohydrochloride with an empirical formula of C9H11Cl3N4and a molecular weight of 281.6. The chemical structure of apraclonidine hydrochloride is:

Each mL of IOPIDINE 1% Ophthalmic Solution contains:

Actives: apraclonidine hydrochloride 11.5 mg equivalent to apraclonidine base
10 mg.

Inactives:sodium chloride, sodium acetate, sodium hydroxide and/or hydrochloric acid (pH 4.4‑7.8), purified water and benzalkonium
chloride 0.01% (preservative). Osmolality is 260‑320 mOsm.

CLINICAL PHARMACOLOGY

Apraclonidine is a relatively selective, alpha adrenergic agonist and does not have significant membrane stabilizing (local anesthetic) activity. When instilled into the eye, IOPIDINE 1% (apraclonidine hydrochloride ophthalmic solution) has the action of reducing intraocular pressure (IOP). Ophthalmic apraclonidine has minimal effect on cardiovascular parameters.

Optic nerve head damage and visual field loss may result from an acute elevation in IOP that can occur after argon or Nd:YAG laser surgical procedures. Elevated IOP, whether acute or chronic in duration, is a major risk factor in the pathogenesis of visual field loss. The higher the peak or spike of IOP, the greater the likelihood of visual field loss and optic nerve damage especially in patients with previously compromised optic nerves. The onset of action with IOPIDINE 1% Ophthalmic Solution can usually be noted within one hour and the maximum IOP reduction usually occurs three to five hours after application of a single dose. The precise mechanism of the ocular hypotensive action of IOPIDINE 1% Ophthalmic Solution is not completely established at this time. Aqueous fluorophotometry studies in man suggest that its predominant action may be related to a reduction of aqueous formation. Controlled clinical studies of patients requiring argon laser trabeculoplasty, argon laser iridotomy or Nd:YAG posterior capsulotomy showed that IOPIDINE 1% Ophthalmic Solution controlled or prevented the post-surgical IOP rise typically observed in patients after undergoing those procedures. After surgery, the mean IOP was 1.2 to 4 mmHg below the corresponding pre-surgical baseline pressure before IOPIDINE Ophthalmic Solution treatment. With placebo treatment, post-surgical pressures were 2.5 to 8.4 mmHg higher than their corresponding pre-surgical baselines. Overall, only 2% of patients treated with IOPIDINE* 1% Ophthalmic Solution had severe IOP elevations (spike greater than or equal to 10 mmHg) during the first three hours after laser surgery, whereas 23% of placebo-treated patients responded with severe pressure spikes (Table 1). Of the patients that experienced a pressure spike after surgery, the peak IOP was above 30 mmHg in most patients (Table 2) and was above 50 mmHg in seven placebo-treated patients and one IOPIDINE 1% Ophthalmic Solution-treated patient.

Table 1: Incidence of IOP Spikes Greater Than or Equal to 10 mmHg

Study | Laser Procedure | Treatment
Study | Laser Procedure |  | Apraclonidine |  | Placebo
Study | Laser Procedure | P‑Value | aN | (%) | aN | (%)
1 | Trabeculoplasty | <0.05 | 0/40 | (0%) | 6/35 | (17%)
2 | Trabeculoplasty | =0.06 | 2/41 | (5%) | 8/42 | (19%)
1 | Iridotomy | <0.05 | 0/11 | (0%) | 4/10 | (40%)
2 | Iridotomy | =0.05 | 0/17 | (0%) | 4/19 | (21%)
1 | Nd:YAG Capsulotomy | <0.05 | 3/80 | (4%) | 19/83 | (23%)
2 | Nd:YAG Capsulotomy | <0.05 | 0/83 | (0%) | 22/81 | (27%)

aN = Number Spikes/Number Eyes.

Table 2: Magnitude of Post-surgical IOP in Trabeculoplasty, Iridotomy and Nd:YAG Capsulotomy Patients With Severe Pressure Spikes Greater than or Equal to 10 mmHg

Maximum Postsurgical IOP (mmHg)

Treatment | Total Spikes | 20-29 mmHg | 30-39 mmHg | 40-49 mmHg | > 50 mmHg
IOPIDINE | 8 | 1 | 4 | 2 | 1
Placebo | 78 | 16 | 47 | 8 | 7

INDICATIONS AND USAGE

IOPIDINE 1% Ophthalmic Solution is indicated to control or prevent
post-surgical elevations in IOP that occur in patients after argon laser
trabeculoplasty, argon laser iridotomy or Nd:YAG posterior capsulotomy.

CONTRAINDICATIONS

IOPIDINE 1% Ophthalmic Solution is contraindicated for patients
receiving monoamine oxidase inhibitor therapy and for patients with
hypersensitivity to any component of this medication or to clonidine.

WARNINGS

FOR TOPICAL OPHTHALMIC USE ONLY. Not for injection or oral ingestion.

PRECAUTIONS

GENERAL PRECAUTIONS

Since IOPIDINE* 1% Ophthalmic Solution is a potent depressor of IOP,
patients who develop exaggerated reductions in IOP should be closely
monitored. Although the acute administration of two drops of IOPIDINE
1% Ophthalmic Solution has minimal effect on heart rate or blood
pressure in clinical studies evaluating patients undergoing anterior
segment laser surgery, the preclinical pharmacologic profile of this drug
suggests that caution should be observed in treating patients with severe
cardiovascular disease including hypertension. IOPIDINE 1% Ophthalmic
Solution should also be used with caution in patients with severe
coronary insufficiency, recent myocardial infarction, cerebrovascular
disease, chronic renal failure, Raynaud’s disease or thromboangiitis
obliterans.
The possibility of a vasovagal attack occurring during laser surgery
should be considered and caution used in patients with history of such
episodes.
Topical ocular administration of two drops of 0.5%, 1%, and 1.5%
IOPIDINE Ophthalmic Solution to New Zealand Albino rabbits three times
daily for one month resulted in sporadic and transient instances of
minimal corneal cloudiness in the 1.5% group only. No histopathological changes were noted in those eyes. No adverse ocular effects were
observed in cynomolgus monkeys treated with two drops of 1.5%
IOPIDINE Ophthalmic Solution applied three times daily for three months.
No corneal changes were observed in 320 humans given at least one
dose of IOPIDINE 1% Ophthalmic Solution.

PATIENT COUNSELING INFORMATION

Apraclonidine can cause dizziness and somnolence. Patients who engage
in hazardous activities requiring mental alertness should be warned of the
potential for a decrease in mental alertness on the day of surgery.

Interactions with other agents have not been investigated.

CARCINOGENESIS AND MUTAGENESIS AND IMPAIRMENT OF FERTILITY

No significant change in tumor incidence or type was observed
following two years of oral administration of apraclonidine HCl to rats
and mice at dosages of 1 and 0.6 mg/kg/day, up to 50 and 30 times,
respectively, the maximum dose recommended for human topical
ocular use. Apraclonidine HCl was not mutagenic in a series of in vitro
mutagenicity tests, including the Ames test, a mouse lymphoma forward
mutation assay, a chromosome aberration assay in cultured Chinese
hamster ovary (CHO) cells, a sister chromatid exchange assay in CHO
cells, and a cell transformation assay. An in vivo mouse micronucleus
assay conducted with apraclonidine HCl also provided no evidence of
mutagenicity. Reproduction and fertility studies in rats showed no adverse
effect on male or female fertility at a dose of 0.5 mg/kg/day (25 times the
maximum recommended human dose).

PREGNANCY

Apraclonidine HCl has been shown to have an embryocidal effect in
rabbits when given in an oral dose of 3 mg/kg/day (150 times the
maximum recommended human dose). Dose related maternal toxicity
was observed in pregnant rats at 0.3 mg/kg/day (15 times the maximum
recommended human dose). There are no adequate and well controlled
studies in pregnant women. IOPIDINE* 1% Ophthalmic Solution should be
used during pregnancy only if the potential benefit justifies the potential
risk to the fetus.

NURSING MOTHERS

It is not known if topically applied IOPIDINE 1% Ophthalmic Solution is
excreted in human milk. Decision should be made to discontinue nursing
temporarily for the one day on which IOPIDINE 1% Ophthalmic Solution
is used.

PEDIATRIC USE

Safety and effectiveness in pediatric patients have not been established.

GERIATRIC USE

No overall differences in safety or effectiveness have been observed
between elderly and younger patients.

ADVERSE REACTIONS

The following adverse events, occurring in less than 2% of patients, were
reported in association with the use of IOPIDINE 1% Ophthalmic Solution
in laser surgery: ocular injection, upper lid elevation, irregular heart rate,
nasal decongestion, ocular inflammation, conjunctival blanching, and
mydriasis.
The following adverse events were observed in investigational studies
dosing IOPIDINE 1% Ophthalmic Solution once or twice daily for up to
28 days in non‑laser studies:
Ocular
Conjunctival blanching, upper lid elevation, mydriasis, burning, discomfort,
foreign body sensation, dryness, itching, hypotony, blurred or dimmed
vision, allergic response, conjunctival microhemorrhage.

Gastrointestinal
Abdominal pain, diarrhea, stomach discomfort, emesis
Cardiovascular
Bradycardia, vasovagal attack, palpitations, orthostatic
episode
Central Nervous System
Insomnia, dream disturbances, irritability, decreased libido.
Other
Taste abnormalities, dry mouth, nasal burning or dryness,
headache, head cold sensation, chest heaviness or burning,
clammy or sweaty palms, body heat sensation, shortness
of breath, increased pharyngeal secretion, extremity pain
or numbness, fatigue, paresthesia, pruritus not associated
with rash.
Clinical Practice
The following events have been identified during postmarketing use
of IOPIDINE 1% Ophthalmic Solution in clinical practice. Because they
are reported voluntarily from a population of unknown size, estimates
of frequency cannot be made. The events, which have been chosen for
inclusion due to either their seriousness, frequency of reporting, possible
causal connection to IOPIDINE 1% Ophthalmic Solution, or a combination
of these factors, include hypersensitivity.

OVERDOSAGE

Ingestion of IOPIDINE* 0.5% Ophthalmic Solution has been reported to
cause bradycardia, drowsiness, and hypothermia. Accidental or intentional
ingestion of oral clonidine has been reported to cause apnea, arrhythmias,
asthenia, bradycardia, conduction defects, diminished or absent reflexes,
dryness of the mouth, hypotension, hypothermia, hypoventilation,
irritability, lethargy, miosis, pallor, respiratory depression, sedation
or coma, seizure, somnolence, transient hypertension, and vomiting.
Treatment of an oral overdose includes supportive and symptomatic
therapy; a patent airway should be maintained. Hemodialysis is of limited
value since a maximum of 5% of circulating drug is removed.

DOSAGE AND ADMINISTRATION

One drop of IOPIDINE* 1% Ophthalmic Solution should be instilled in the
scheduled operative eye one hour before initiating anterior segment
laser surgery and a second drop should be instilled to the same eye
immediately upon completion of the laser surgical procedure. Use
a separate container for each single‑drop dose and discard each
container after use.

HOW SUPPLIED

IOPIDINE 1% Ophthalmic Solution as base is a sterile, isotonic, aqueous
solution containing apraclonidine hydrochloride.
Supplied as follows: 0.1 mL in plastic ophthalmic dispensers, packaged
two per pouch. These dispensers are enclosed in a foil overwrap as an
added barrier to evaporation.
0.1 mL (packaged two per pouch) NDC 82667‑200-01

Storage:Store at 2°C to 25°C (36°F‑77°F).
Protect from light.

Manufactured for:
Harrow Eye, LLC™
Nashville, TN 37205 USA
Revised: February 2023

PACKAGE LABEL

NDC 82667-200-01
IOPIDINE®
(apraclonide hydrochloride ophthalmic solution)

1% as base
Sterile
CONTENTS: 12 pouches containing 2 units, 0.1mL each
Store at 2°-25°C (36°-77°F). Protect from light.

Rx Only

HARROW®
Manufactured for:
Harrow Eye, LLC,
Nashville, TN 37205 USA
Made in France